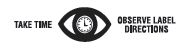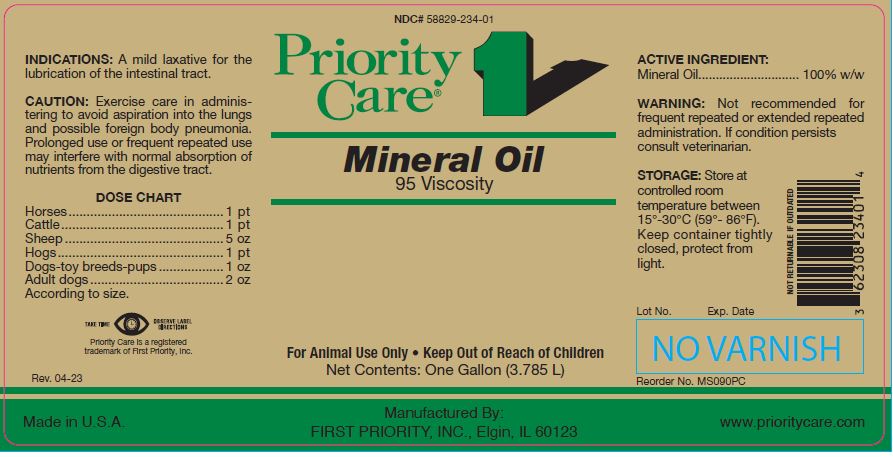 DRUG LABEL: Mineral Oil
NDC: 58829-234 | Form: LIQUID
Manufacturer: FIRST PRIORITY INCORPORATED
Category: animal | Type: OTC ANIMAL DRUG LABEL
Date: 20260223

ACTIVE INGREDIENTS: MINERAL OIL 854.5 g/1 L

Mineral Oil
95 Viscosity

KEEP OUT OF REACH OF CHILDREN

For Animal Use Only
Keep Out of Reach of Children

INDICATIONS:

A mild laxative for the lubrication of the intestinal tract.

CAUTION:

Exercise care in administering to avoid aspiration into the lungs and possible foreign body pneumonia. Prolonged use or frequent repeated use may interfere with normal absorption of nutrients from the digestive tract.

DOSE CHART:

Horses........................................... 1 pt
Cattle............................................. 1 pt
Sheep ............................................ 5 oz
Hogs.............................................. 1 pt
Dogs-toy breeds-pups .................. 1 oz
Adult dogs ..................................... 2 oz
According to size.

ACTIVE INGREDIENT:

Mineral Oil............................. 100% w/w

WARNING:

Not recommended for frequently repeated or extended repeated administration. If condition persists consult a veterinarian.

STORAGE:

Store at controlled room temperature between 15º to 30ºC (59º-86ºF). Keep tightly closed, protect from light.

Net Contents:

One Gallon (3.785 L) Reorder No. MS090PC

INFORMATION FOR OWNERS/CAREGIVERS

Priority Care is a registered trademark of First Priority, Inc.

Made in U.S.A.

Manufactured By: FIRST PRIORITY, INC., Elgin, IL 60123

www.prioritycare.com

NOT RETURNABLE IF OUTDATED